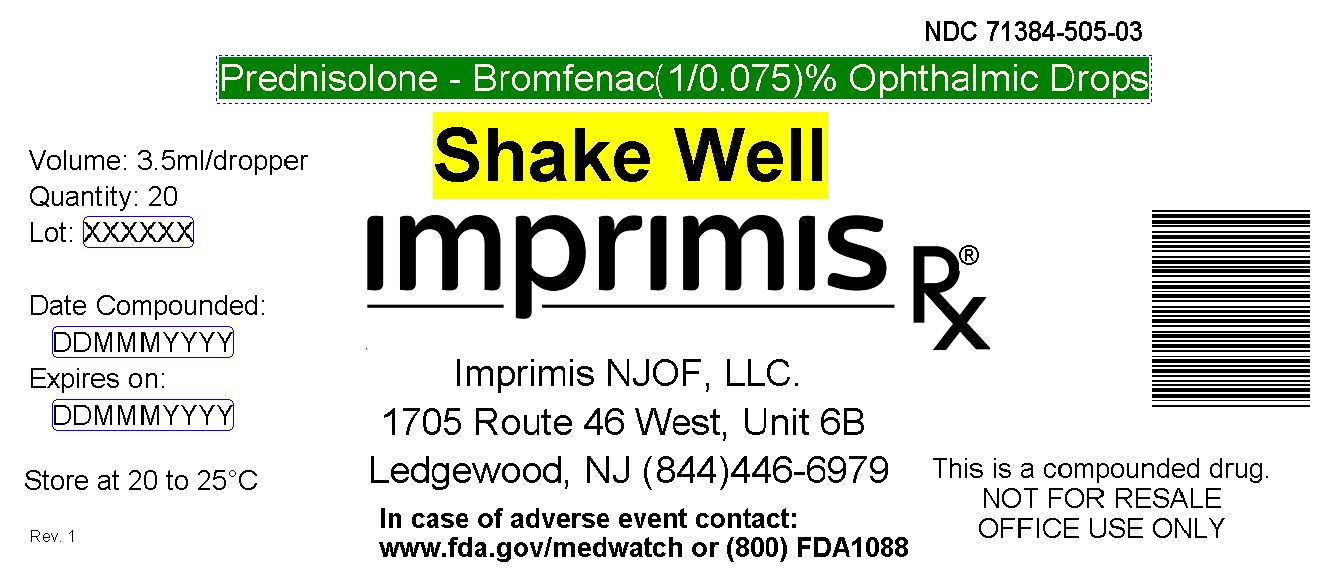 DRUG LABEL: Pred-Brom
NDC: 71384-505 | Form: SUSPENSION/ DROPS
Manufacturer: Imprimis NJOF, LLC
Category: prescription | Type: HUMAN PRESCRIPTION DRUG LABEL
Date: 20180119

ACTIVE INGREDIENTS: PREDNISOLONE ACETATE 10 mg/1 mL; BROMFENAC SODIUM 0.75 mg/1 mL

STORAGE AND HANDLING

Store at 20° to 25° C (68° to 77° F)